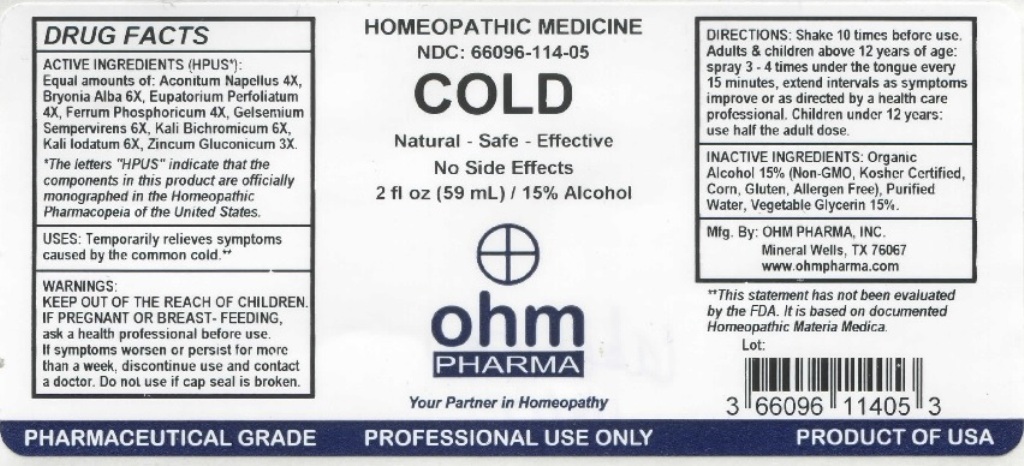 DRUG LABEL: Cold
NDC: 66096-114 | Form: LIQUID
Manufacturer: OHM PHARMA INC.
Category: homeopathic | Type: HUMAN OTC DRUG LABEL
Date: 20211229

ACTIVE INGREDIENTS: ACONITUM NAPELLUS 4 [hp_X]/59 mL; BRYONIA ALBA ROOT 6 [hp_X]/59 mL; EUPATORIUM PERFOLIATUM FLOWERING TOP 4 [hp_X]/59 mL; FERROSOFERRIC PHOSPHATE 4 [hp_X]/59 mL; GELSEMIUM SEMPERVIRENS ROOT 6 [hp_X]/59 mL; POTASSIUM DICHROMATE 6 [hp_X]/59 mL; POTASSIUM IODIDE 6 [hp_X]/59 mL; ZINC GLUCONATE 3 [hp_X]/59 mL
INACTIVE INGREDIENTS: ALCOHOL; WATER; GLYCERIN

OHM Cold

ACTIVE INGREDIENT

ACTIVE INGREDIENTS (HPUS*): Equal amounts of: Aconitum Napellus 4X, Bryonia Alba 6X, Eupatorium Perfoliatum 4X, Ferrum Phosphoricum 4X, Gelsemium Sempervirens 6X, Kali Bichromicum 6X, Kali lodatum 6X, Zincum Gluconicum 3X.

*The letters "HPUS" indicate that the components in this product are officially monographed in the Homeopathic Pharmacopeia of the United States.

INDICATIONS AND USAGE

USES: Temporarily relieves symptoms caused by the common cold.**

**This statement has not been evaluated by the FDA. It is based on documented Homeopathic Materia Medica.

WARNINGS

WARNINGS: IF PREGNANT OR BREAST-FEEDING, ask a health professional before use. If symptoms worsen or persist for more than a week, discontinue use and contact a doctor.

- KEEP OUT OF REACH OF CHILDREN.

DOSAGE AND ADMINISTRATION

DIRECTIONS: Shake 10 times before use. Adults & children above 12 years of age: spray 3-4 times under the tongue every 15 minutes, extend intervals as symptoms improve or as directed by a health care professional. Children under 12: use half the adult dose.

Do not use if cap seal is broken.

INACTIVE INGREDIENT

INACTIVE INGREDIENTS: Ethanol Alcohol 15% (Non-GMO, Kosher Certified, Corn, Gluten, Allergen Free), Purified Water, Vegetable Glycerin 15%.

QUESTIONS

Mfg. By: OHM PHARMA, INC. Mineral Wells, TX 76067

www.ohmpharma.com

PACKAGE LABEL

HOMEOPATHIC MEDICINE

NDC: 66096-114-05

COLD

Natural - Safe - Effective

No Side Effects

2 fl oz (59mL) / 15% Alcohol

PRODUCT OF USA

PURPOSE

Temporarily relieves symptoms caused by the common cold.